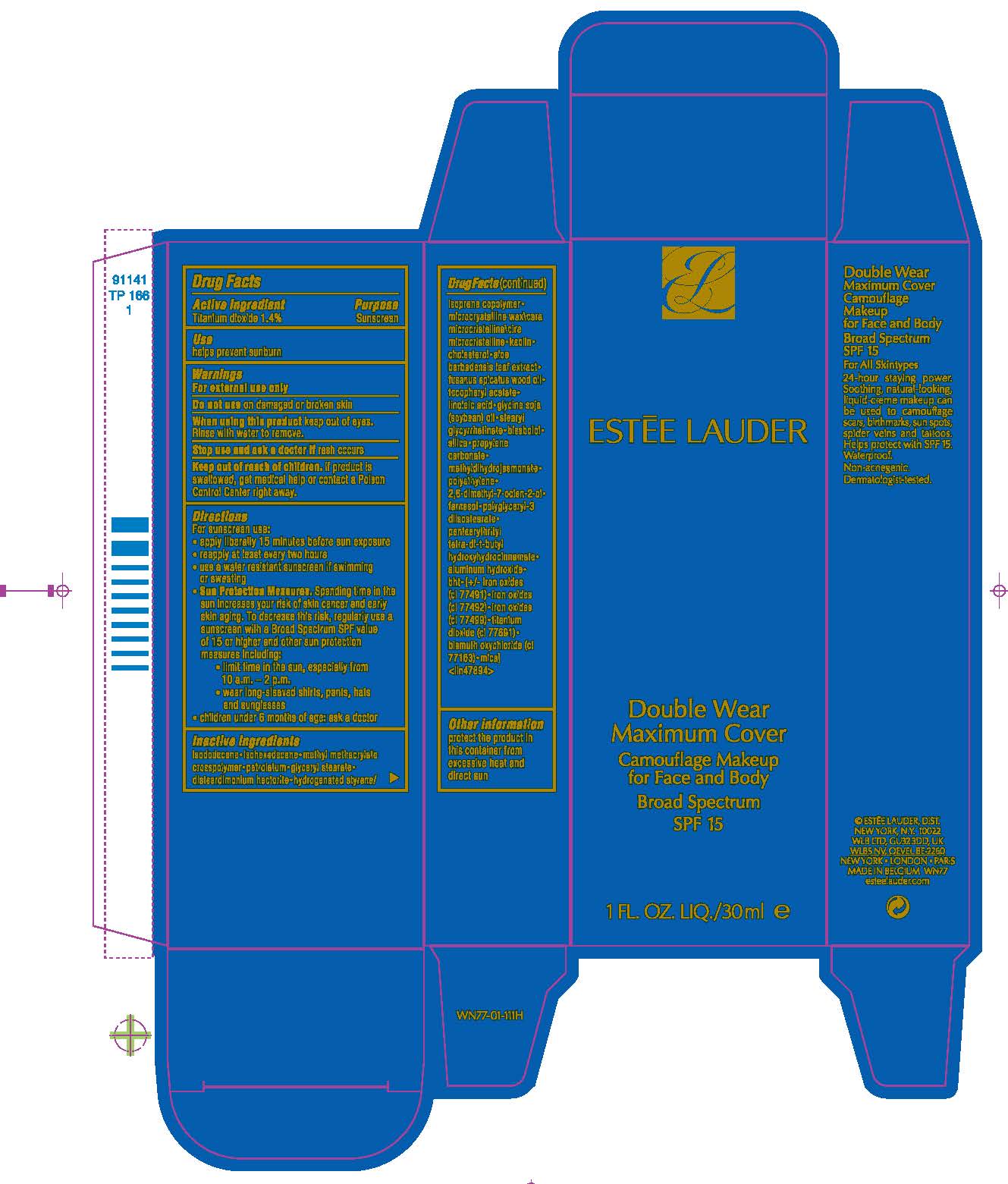 DRUG LABEL: DOUBLE WEAR MAXIMUM COVER CAMOUFLAGE MAKEUP FOR FACE AND BODY BROAD SPECTRUM SPF 15
NDC: 11559-030 | Form: CREAM
Manufacturer: ESTEE LAUDER INC
Category: otc | Type: HUMAN OTC DRUG LABEL
Date: 20241225

ACTIVE INGREDIENTS: TITANIUM DIOXIDE 14 mg/1 mL
INACTIVE INGREDIENTS: FARNESOL; ALUMINUM HYDROXIDE; ISODODECANE; ISOHEXADECANE; METHYL METHACRYLATE/GLYCOL DIMETHACRYLATE CROSSPOLYMER; PETROLATUM; GLYCERYL MONOSTEARATE; DISTEARDIMONIUM HECTORITE; MICROCRYSTALLINE WAX; KAOLIN; CHOLESTEROL; ALOE VERA LEAF; SANTALUM SPICATUM OIL; LINOLEIC ACID; SOYBEAN OIL; STEARYL GLYCYRRHETINATE; LEVOMENOL; SILICON DIOXIDE; PROPYLENE CARBONATE; METHYL DIHYDROJASMONATE (SYNTHETIC); HIGH DENSITY POLYETHYLENE; DIHYDROMYRCENOL; POLYGLYCERYL-3 DIISOSTEARATE; PENTAERYTHRITOL TETRAKIS(3-(3,5-DI-TERT-BUTYL-4-HYDROXYPHENYL)PROPIONATE); FERRIC OXIDE RED; FERRIC OXIDE YELLOW; FERROSOFERRIC OXIDE; MICA; BISMUTH OXYCHLORIDE; BUTYLATED HYDROXYTOLUENE

DOUBLE WEAR MAXIMUM COVER CAMOUFLAGE MAKEUP FOR FACE AND BODY BROAD SPECTRUM SPF 15

Drug Facts

Active ingredient

Titanium dioxide 1.40%

Purpose

Sunscreen

Use

helps prevent sunburn

Warnings

For external use only

Do not use on damaged or broken skin

When using this product keep out of eyes. Rinse with water to remove.

Stop use and ask a doctor if rash occurs

Keep out of reach of children. If product is swallowed, get medical help or contact a Poison Control Center right away.

Directions

For sunscreen use:

- apply liberally 15 minutes before sun exposure
- reapply at least every two hours
- use a water resistant sunscreen if swimming or sweating
- Sun Protection Measures. Spending time in the sun increases your risk of skin cancer and early skin aging. To decrease the risk, regularly use a sunscreen with a Broad Spectrum SPF value of 15 or higher and other sun protection measures including:
  - limit time in the sun, especially from 10 a.m. – 2 p.m.
  - wear long-sleeved shirts, pants, hats and sunglasses
- children under 6 months of age: ask a doctor

Inactive ingredients

isododecane•isohexadecane•methyl methacrylate crosspolymer•petrolatum•glyceryl stearate•disteardimonium hectorite•hydrogenated styrene/isoprene copolymer•microcrystalline wax\cera microcristallina\cire microcristalline•kaolin•cholesterol•aloe barbadensis leaf extract•fusanus spicatus wood oil•tocopheryl acetate•linoleic acid•glycine soja (soybean) oil•stearyl glycyrrhetinate•bisabolol•silica•propylene carbonate•methyldihydrojasmonate•polyethylene•2,6-dimethyl-7-octen-2-ol•polyglyceryl-3 diisostearate•pentaerythrityl tetra-di-t-butyl hydroxyhydrocinnamate• alumina•phenethyl alcohol•[+/- iron oxides (ci 77491)•iron oxides (ci 77492)•iron oxides (ci 77499)•titanium dioxide (ci 77891)•mica•bismuth oxychloride (ci 77163)] <iln40794>

Other information

protect the product in this container from excessive heat and direct sun

PRINCIPAL DISPLAY PANEL - 30 ml Tube Carton

ESTĒE LAUDER

Double Wear
Maximum Cover

Camouflage Makeup
for Face and Body

Broad Spectrum
SPF 15

1 FL. OZ. LIQ./30 ml e